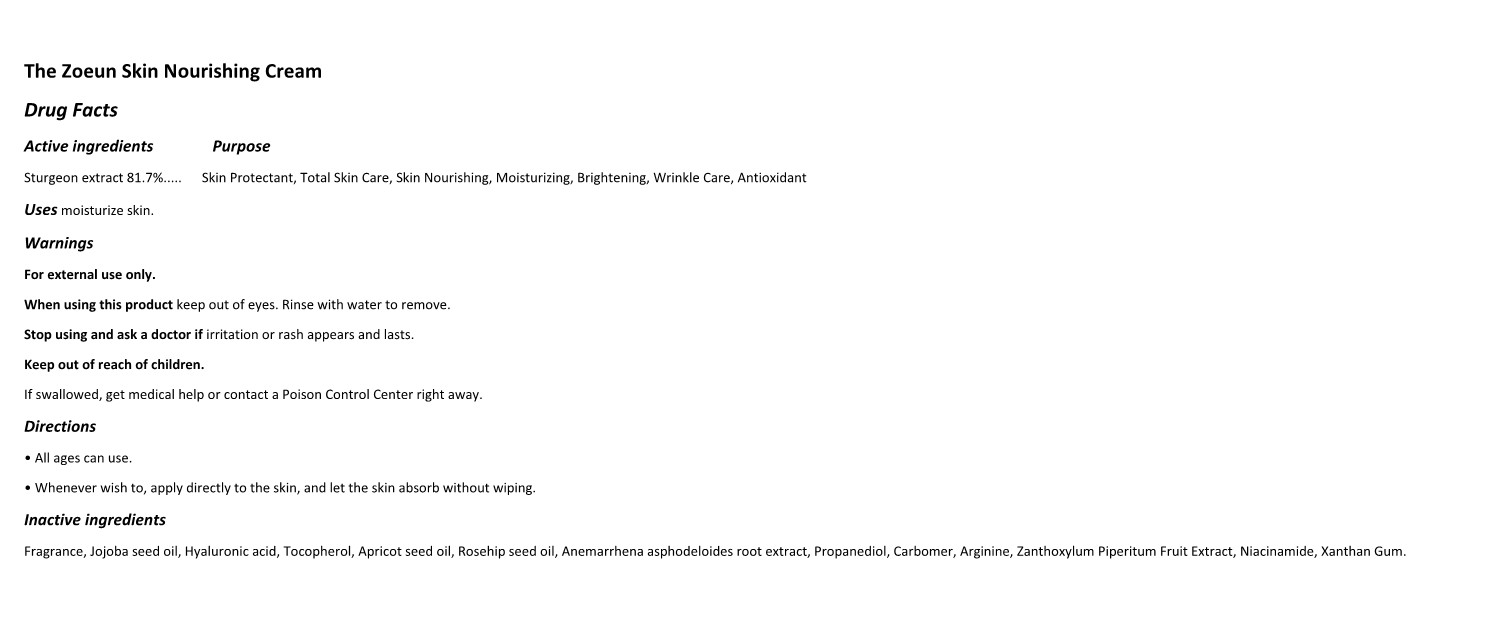 DRUG LABEL: The Zoeun Skin Nourishing Cream
NDC: 83636-701 | Form: CREAM
Manufacturer: Sturgeonbio Co.,Ltd
Category: otc | Type: HUMAN OTC DRUG LABEL
Date: 20250120

ACTIVE INGREDIENTS: STURGEON, UNSPECIFIED 81.7 g/100 mL
INACTIVE INGREDIENTS: FRAGRANCE 13576; APRICOT KERNEL OIL; WATER; FISH OIL; 1,2-HEXANEDIOL; JOJOBA OIL; ZANTHOXYLUM PIPERITUM FRUIT PULP; XANTHAN GUM; ROSA CANINA SEED; PROPANEDIOL; ACETYL ARGININE; ANEMARRHENA ASPHODELOIDES ROOT; TOCOPHEROL; CARBOXYPOLYMETHYLENE; BUTYLENE GLYCOL; HYALURONATE SODIUM; NIACINAMIDE

83636-701 The Zoeun Skin Nourishing Cream

Active Ingredients

Sturgeon extract 81.7%

Purposes

Skin Protectant, Total Skin Care, Skin Nourishing, Moisturizing, Brightening, Wrinkle Care, Antioxidant

Uses

Skin Nourishing, Moisturizing, Brightening, Wrinkle Care

Warnings

Keep out of reach of children.
If swallowed, get medical help or contact a Poison Control Center right away.

Warnings

Stop using and ask a doctor if irritation or rash appears and lasts.

Warnings

When using this product keep out of eyes. Rinse with water to remove

Warnings

For external use only.

Directions

• All ages can use.
• Whenever wish to, apply directly to the skin, and let the skin absorb without wiping.

Inactive Ingredients

Fragrance, Jojoba seed oil, Hyaluronic acid, Tocopherol, Apricot seed oil, Rosehip seed oil, Anemarrhena asphodeloides root extract, Propanediol, Carbomer, Arginine, Zanthoxylum Piperitum Fruit Extract, Niacinamide, Xanthan Gum